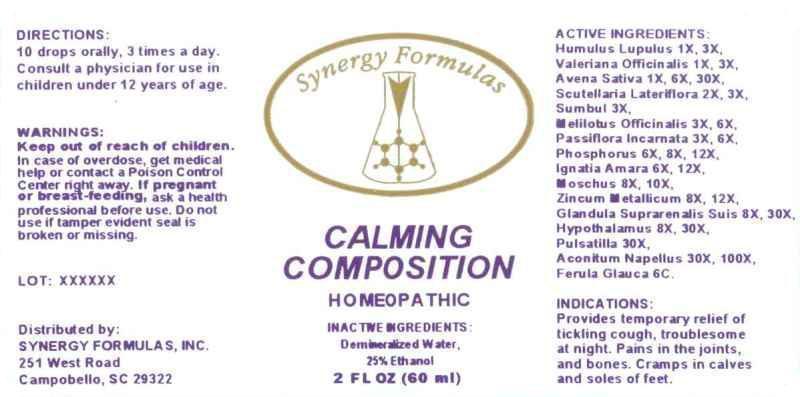 DRUG LABEL: CALMING COMPOSITION
NDC: 43772-0044 | Form: LIQUID
Manufacturer: Synergy Formulas, Inc.
Category: homeopathic | Type: HUMAN OTC DRUG LABEL
Date: 20141117

ACTIVE INGREDIENTS: HOPS 1 [hp_X]/1 mL; VALERIAN 1 [hp_X]/1 mL; AVENA SATIVA FLOWERING TOP 1 [hp_X]/1 mL; SCUTELLARIA LATERIFLORA 2 [hp_X]/1 mL; FERULA SUMBUL ROOT 3 [hp_X]/1 mL; MELILOTUS OFFICINALIS TOP 3 [hp_X]/1 mL; PASSIFLORA INCARNATA FLOWERING TOP 3 [hp_X]/1 mL; PHOSPHORUS 6 [hp_X]/1 mL; STRYCHNOS IGNATII SEED 6 [hp_X]/1 mL; MOSCHUS MOSCHIFERUS MUSK SAC RESIN 8 [hp_X]/1 mL; ZINC 8 [hp_X]/1 mL; SUS SCROFA ADRENAL GLAND 8 [hp_X]/1 mL; SUS SCROFA HYPOTHALAMUS 8 [hp_X]/1 mL; PULSATILLA VULGARIS 30 [hp_X]/1 mL; ACONITUM NAPELLUS 30 [hp_X]/1 mL; FERULA COMMUNIS SUBSP. GLAUCA 6 [hp_C]/1 mL
INACTIVE INGREDIENTS: WATER; ALCOHOL

DRUG FACTS:

ACTIVE INGREDIENTS:

HUMULUS LUPULUS 1X, 3X, VALERIANA OFFICINALIS 1X, 3X, AVENA SATIVA 1X, 6X, 30X, SCUTELLARIA LATERIFLORA 2X, 3X, SUMBUL 3X, MELILOTUS OFFICINALIS 3X, 6X, PASSIFLORA INCARNATA 3X, 6X, PHOSPHORUS 6X, 8X, 12X, IGNATIA AMARA 6X, 12X, MOSCHUS 8X, 10X, ZINCUM METALLICUM 8X, 12X, GLANDULA SUPRARENALIS SUIS 8X, 30X, HYPOTHALAMUS (SUIS) 8X, 30X, PULSATILLA (VULGARIS) 30X, ACONITUM NAPELLUS 30X, 100X, FERULA GLAUCA 6C

INDICATIONS:

Provides temporary relief of tickling cough, troublesome at night. Pains in the joints, and bones. Cramps in calves and soles of feet.

WARNINGS:

Keep out of reach of children. In case of overdose, get medical help or contact a Poison Control Center right away.

If pregnant or breast-feeding, ask a health professional before use.

Do not use if tamper evident seal is broken or missing.

Keep out of reach of children. In case of overdose, get medical help or contact a Poison Control Center right away.

DIRECTIONS:

10 drops orally, 3 times a day. Consult a physician for use in children under 12 years of age.

INDICATIONS:

Provides temporary relief of tickling cough, troublesome at night. Pains in the joints, and bones. Cramps in calves and soles of feet.

INACTIVE INGREDIENTS:

Demineralized Water, 25% Ethanol

QUESTIONS:

Distributed by:

SYNERGY FORMULAS, INC.

251 West Road

Campobello, SC 29322

PACKAGE LABEL DISPLAY:

Synergy Formulas

CALMING COMPOSITION

HOMEOPATHIC

2 FL OZ (60 ml)